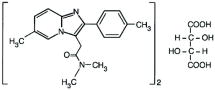 DRUG LABEL: Unknown
Manufacturer: Yung Shin Pharmaceutical Industries, Co., LTD.
Category: prescription | Type: HUMAN PRESCRIPTION DRUG LABEL WITH HIGHLIGHTS
Date: 20070713
DEA Schedule: CIV

HIGHLIGHTS OF PRESCRIBING INFORMATION

Zolpidem tartrate tablets for oral administration

RECENT MAJOR CHANGES

Indications and Usage (1) 03/2007

Warnings and Precautions (5) 03/2007

1 INDICATIONS AND USAGE

Zolpidem tartrate tablets are indicated for the short-term treatment of insomnia characterized by difficulties with sleep initiation. Zolpidem tartrate tablets have been shown to decrease sleep latency for up to 35 days in controlled clinical studies. (1)

2 DOSAGE AND ADMINISTRATION

- Adult dose: 10 mg immediately before bedtime (2.1)
- Elderly/Debilitated patients/Hepatic Impairment: Initial dose of 5 mg (2.2)
- Downward dosage adjustment may be necessary when used with CNS depressants (2.3)
- Total daily dose should not exceed 10 mg (2.4)

3 DOSAGE FORMS AND STRENGTHS

5 mg and 10 mg tablets (3)

4 CONTRAINDICATIONS

Hypersensitivity to zolpidem tartrate or inactive ingredients (4.1)

5 WARNINGS AND PRECAUTIONS

- Reevaluate if insomnia persists after 7 to 10 days of use (5.1)
- Severe anaphylactic and anaphylactoid reactions have been reported (5.2)
- Abnormal thinking, behavior changes and complex behaviors such as sleep-driving have been reported (5.3)
- Pediatric patients with attention-deficit/hyperactivity disorder (ADHD): Hallucinations (7.4%) and other psychiatric and /or nervous system adverse events were observed frequently (5.6, 8.4)
- Depression: Worsening of depression or, suicidal thinking may occur. Prescribe the least amount feasible to avoid intentional overdose (5.3, 5.6)
- Withdrawal symptoms may occur with rapid dose reduction or discontinuation (5.4)
- CNS depressant effects, additive effects with CNS depressants (2.3, 5.5)
- Potential impairment of activities requiring complete mental alertness such as operating machinery or driving a motor vehicle, after ingesting the drug and the following day (5.5)
- Additive effects with alcohol; should not be taken with alcohol (5.5)
- Elderly/debilitated patients: Impaired motor, cognitive performance after repeated exposure, increased sensitivity (2.2, 5.6)
- Caution advised in patients with hepatic impairment, mild to moderate COPD, impaired drug metabolism or hemodynamic responses, mild to moderate sleep apnea (5.6)

6 ADVERSE REACTIONS

- Most commonly observed adverse events in studies with zolpidem (up to 10 mg) at statistically significant differences from placebo were:
  Short-term (<10 nights): Drowsiness, dizziness, and diarrhea
  Long-term (28 - 35 nights): Dizziness and drugged feelings (6.1)
- Dose relationship observed for adverse events especially CNS and GI events (6.1)
- Other adverse reactions, including serious adverse reactions, have been reported (6)

7 DRUG INTERACTIONS

- Imipramine: decreased alertness (7.1)
- Chlorpromazine: impaired alertness and psychomotor performance (7.1)
- Alcohol causes additive psychomotor impairment (7.1)
- Rifampin (CYP450) decreases exposure to, and effects of zolpidem (7.2)
- Sedative/hypnotic effect reversed by flumazenil (7.3, 10.2)

8 USE IN SPECIFIC POPULATIONS

- Labor and delivery: No established use (8.2)
- Nursing mothers: Not recommended (8.3)
- Pediatric use: Safety and effectiveness have not been established (8.4)
- Geriatric use: Reduced dose in elderly to decrease side effects (8.5)

FULL PRESCRIBING INFORMATION

1 INDICATIONS AND USAGE

Zolpidem tartrate tablets are indicated for the short-term treatment of insomnia characterized by difficulties with sleep initiation. Zolpidem tartrate tablets have been shown to decrease sleep latency for up to 35 days in controlled clinical studies [see Clinical Studies (14)].

The clinical trials performed in support of efficacy were 4-5 weeks in duration with the final formal assessments of sleep latency performed at the end of treatment.

2 DOSAGE AND ADMINISTRATION

2.1 Dosage in adults

The dose of zolpidem tartrate tablets should be individualized.

The recommended dose for adults is 10 mg immediately before bedtime.

2.2 Special Populations

Elderly or debilitated patients may be especially sensitive to the effects of zolpidem tartrate tablets . Patients with hepatic insufficiency do not clear the drug as rapidly as normals. An initial 5 mg dose is recommended in these patients [see Warnings and Precautions (5)].

2.3 Administration with CNS depressants:

Downward dosage adjustment may be necessary when zolpidem tartrate tablets is administered with agents having known CNS-depressant effects because of the potentially additive effects [see Warnings and Precautions (5)].

2.4 Maximum daily dose:

The total zolpidem tartrate tablets dose should not exceed 10 mg per day.

3 DOSAGE FORMS AND STRENGTHS

Zolpidem tartrate tablets are available in 5 mg and 10 mg strength tablets for oral administration.

Zolpidem tartrate tablets 5-mg are white round film-coated tablets engraved with “CST 8”. Zolpidem tartrate tablets 10-mg are white round film-coated tablets engraved with “B”. Tablets are not scored.

4 CONTRAINDICATIONS

4.1 Hypersensitivity

Zolpidem tartrate tablets are contraindicated in patients with known hypersensitivity to zolpidem tartrate or to any of the inactive ingredients in the formulation.

5 WARNINGS AND PRECAUTIONS

5.1 General

Because sleep disturbances may be the presenting manifestation of a physical and/or psychiatric disorder, symptomatic treatment of insomnia should be initiated only after a careful evaluation of the patient. The failure of insomnia to remit after 7 to 10 days of treatment may indicate the presence of a primary psychiatric and/or medical illness that should be evaluated.

Worsening of insomnia or the emergence of new thinking or behavior abnormalities may be the consequence of an unrecognized psychiatric or physical disorder. Such findings have emerged during the course of treatment with sedative/hypnotic drugs, including zolpidem tartrate tablets. Because some of the important adverse effects of zolpidem tartrate tablets appear to be dose related [see Dosage and Administration (2)], it is important to use the smallest possible effective dose, especially in the elderly.

5.2 Severe anaphylactic and anaphylactoid reactions

Rare cases of angioedema involving the tongue, glottis or larynx have been reported in patients after taking the first or subsequent doses of sedative-hypnotics, including zolpidem tartrate tablets. Some patients have had additional symptoms such as dyspnea, throat closing or nausea and vomiting that suggest anaphylaxis. Some patients have required medical therapy in the emergency department. If angioedema involves the throat, glottis or larynx, airway obstruction may occur and be fatal. Patients who develop angioedema after treatment with zolpidem tartrate tablets should not be rechallenged with the drug.

5.3 Abnormal Thinking and Behavioral Changes

A variety of abnormal thinking and behavior changes have been reported to occur in association with the use of sedative/hypnotics. Some of these changes may be characterized by decreased inhibition (eg, aggressiveness and extroversion that seemed out of character), similar to effects produced by alcohol and other CNS depressants. Visual and auditory hallucinations have been reported as well as behavioral changes such as bizarre behavior, agitation and depersonalization. In controlled trials, <1% of adults with insomnia who received zolpidem reported hallucinations. In a clinical trial, 7.4 % of pediatric patients with insomnia associated with attention-deficit/hyperactivity disorder (ADHD), who received zolpidem reportedhallucinations.

Complex behaviors such as “sleep-driving” (i.e., driving while not fully awake after ingestion of a sedative-hypnotic, with amnesia for the event) have been reported. These events can occur in sedative-hypnotic-naive as well as in sedative-hypnotic-experienced persons. Although behaviors such as “sleep-driving” may occur with zolpidem tartrate tablets alone at therapeutic doses, the use of alcohol and other CNS depressants with zolpidem tartrate tablets appears to increase the risk of such behaviors, as does the use of zolpidem tartrate tablets at doses exceeding the maximum recommended dose. Due to the risk to the patient and the community, discontinuation of zolpidem tartrate tablets should be strongly considered for patients who report a “sleep-driving” episode. Other complex behaviors (e.g., preparing and eating food, making phone calls, or having sex) have been reported in patients who are not fully awake after taking a sedative-hypnotic. As with “sleep-driving”, patients usually do not remember these events. Amnesia, anxiety and other neuro-psychiatric symptoms may occur unpredictably. In primarily depressed patients, worsening of depression, including suicidal thinking, has been reported in association with the use of sedative/hypnotics.

It can rarely be determined with certainty whether a particular instance of the abnormal behaviors listed above is drug induced, spontaneous in origin, or a result of an underlying psychiatric or physical disorder. Nonetheless, the emergence of any new behavioral sign or symptom of concern requires careful and immediate evaluation.

5.4 Withdrawal effects

Following the rapid dose decrease or abrupt discontinuation of sedative/hypnotics, there have been reports of signs and symptoms similar to those associated with withdrawal from other CNS depressant drugs [see Drug Abuse and Dependence (9)].

5.5 CNS depressant effects

Zolpidem tartrate tablets, like other sedative/hypnotic drugs, have CNS-depressant effects. Due to the rapid onset of action, zolpidem tartrate tablets should only be ingested immediately prior to going to bed. Patients should be cautioned against engaging in hazardous occupations requiring complete mental alertness or motor coordination such as operating machinery or driving a motor vehicle after ingesting the drug, including potential impairment of the performance of such activities that may occur the day following ingestion of zolpidem tartrate tablets. Zolpidem tartrate tablets showed additive effects when combined with alcohol and should not be taken with alcohol. Patients should also be cautioned about possible combined effects with other CNS-depressant drugs. Dosage adjustments may be necessary when zolpidem tartrate tablets are administered with such agents because of the potentially additive effects.

5.6 Special Populations

Use in the elderly and/or debilitated patients: Impaired motor and/or cognitive performance after repeated exposure or unusual sensitivity to sedative/hypnotic drugs is a concern in the treatment of elderly and/or debilitated patients. Therefore, the recommended zolpidem tartrate tablets dosage is 5 mg in such patients [see Dosage and Administration (2)] to decrease the possibility of side effects. These patients should be closely monitored.

Use in patients with concomitant illness: Clinical experience with zolpidem tartrate tablets (zolpidem tartrate) in patients with concomitant systemic illness is limited. Caution is advisable in using zolpidem tartrate tablets in patients with diseases or conditions that could affect metabolism or hemodynamic responses. Although studies did not reveal respiratory depressant effects at hypnotic doses of zolpidem tartrate tablets in normals or in patients with mild to moderate chronic obstructive pulmonary disease (COPD), a reduction in the Total Arousal Index together with a reduction in lowest oxygen saturation and increase in the times of oxygen desaturation below 80% and 90% was observed in patients with mild-to-moderate sleep apnea when treated with zolpidem tartrate tablets (10 mg) when compared to placebo. However, precautions should be observed if zolpidem tartrate tablets are prescribed to patients with compromised respiratory function, since sedative/hypnotics have the capacity to depress respiratory drive. Post-marketing reports of respiratory insufficiency, most of which involved patients with pre-existing respiratory impairment, have been received. Data in end-stage renal failure patients repeatedly treated with zolpidem tartrate tablets did not demonstrate drug accumulation or alterations in pharmacokinetic parameters. No dosage adjustment in renally impaired patients is required; however, these patients should be closely monitored [see Pharmacokinetics (12.3)]. A study in subjects with hepatic impairment did reveal prolonged elimination in this group; therefore, treatment should be initiated with 5 mg in patients with hepatic compromise, and they should be closely monitored.

Use in depression: As with other sedative/hypnotic drugs, zolpidem tartrate tablets should be administered with caution to patients exhibiting signs or symptoms of depression. Suicidal tendencies may be present in such patients and protective measures may be required. Intentional over-dosage is more common in this group of patients; therefore, the least amount of drug that is feasible should be prescribed for the patient at any one time.

Pediatric patients: Safety and effectiveness of zolpidem has not been established in pediatric patients. In an 8-week study in pediatric patients (aged 6-17 years) with insomnia associated with ADHD, zolpidem did not decrease sleep latency compared to placebo. Hallucinations were reported in 7.4% of the pediatric patients who received zolpidem; none of the pediatric patients who received placebo reported hallucinations [see Use in Specific Populations: Pediatric Use (8.4)].

5.7 Laboratory tests

Monitoring: There are no specific laboratory tests recommended to monitor zolpidem levels.

Interference with laboratory tests: Zolpidem is not known to interfere with commonly employed clinical laboratory tests. In addition, clinical data indicate that zolpidem does not cross-react with benzodiazepines, opiates, barbiturates, cocaine, cannabinoids, or amphetamines in two standard urine drug screens.

6 ADVERSE REACTIONS

Serious adverse reactions including severe anaphylactic and anaphylactoid reactions, abnormal thinking and behavior, complex behaviors, withdrawal effects, amnesia, anxiety, other neuropsychiatric symptoms and CNS-depressant effects have been reported with zolpidem [see Warnings and Precautions (5)].

6.1 Incidence in controlled clinical trials

Associated with discontinuation of treatment: Approximately 4% of 1,701 patients who received zolpidem at all doses (1.25 to 90 mg) in U.S. premarketing clinical trials discontinued treatment because of an adverse clinical event. Events most commonly associated with discontinuation from U.S. trials were daytime drowsiness (0.5%), dizziness (0.4%), headache (0.5%), nausea (0.6%), and vomiting (0.5%).

Approximately 4% of 1,959 patients who received zolpidem at all doses (1 to 50 mg) in similar foreign trials discontinued treatment because of an adverse event. Events most commonly associated with discontinuation from these trials were daytime drowsiness (1.1%), dizziness/vertigo (0.8%), amnesia (0.5%), nausea (0.5%), headache (0.4%), and falls (0.4%).

Data from a clinical study in which selective serotonin reuptake inhibitor- (SSRI) treated patients were given zolpidem revealed that four of the seven discontinuations during double-blind treatment with zolpidem (n=95) were associated with impaired concentration, continuing or aggravated depression, and manic reaction; one patient treated with placebo (n =97) was discontinued after an attempted suicide.

Most commonly observed adverse events in controlled trials: During short-term treatment (up to 10 nights) with zolpidem tartrate tablets at doses up to 10 mg, the most commonly observed adverse events associated with the use of zolpidem and seen at statistically significant differences from placebo-treated patients were drowsiness (reported by 2% of zolpidem patients), dizziness (1%), and diarrhea (1%). During longer-term treatment (28 to 35 nights) with zolpidem at doses up to 10 mg, the most commonly observed adverse events associated with the use of zolpidem and seen at statistically significant differences from placebo-treated patients were dizziness (5%) and drugged feelings (3%).

Adverse events observed at an incidence of ≥1% in controlled trials: The following tables enumerate treatment-emergent adverse event frequencies that were observed at an incidence equal to 1% or greater among patients with insomnia who received zolpidem tartrate tablets in U.S. placebo-controlled trials. Events reported by investigators were classified utilizing a modified World Health Organization (WHO) dictionary of preferred terms for the purpose of establishing event frequencies. The prescriber should be aware that these figures cannot be used to predict the incidence of side effects in the course of usual medical practice, in which patient characteristics and other factors differ from those that prevailed in these clinical trials. Similarly, the cited frequencies cannot be compared with figures obtained from other clinical investigators involving related drug products and uses, since each group of drug trials is conducted under a different set of conditions. However, the cited figures provide the physician with a basis for estimating the relative contribution of drug and nondrug factors to the incidence of side effects in the population studied.

The following table was derived from a pool of 11 placebo-controlled short-term U.S. efficacy trials involving zolpidem in doses ranging from 1.25 to 20 mg. The table is limited to data from doses up to and including 10 mg, the highest dose recommended for use.

Incidence of Treatment-Emergent Adverse Experiences in Short-term Placebo-Controlled Clinical Trials (Percentage of patients reporting)
Body System/ Adverse Event* | Zolpidem (≤10mg) (N=685) | Placebo (N=473)
Central and Peripheral Nervous System
Headache | 7 | 6
Drowsiness | 2 | _
Dizziness | 1 | _
Gastrointestinal System
Nausea | 2 | 3
Diarrhea | 1 | -
Musculoskeletal System
Myalgia | 1 | 2
*Events reported by at least 1% of Zolpidem patients are included

The following table was derived from a pool of three placebo-controlled long-term efficacy trials involving zolpidem tartrate tablets. These trials involved patients with chronic insomnia who were treated for 28 to 35 nights with zolpidem at doses of 5, 10, or 15 mg. The table is limited to data from doses up to and including 10 mg, the highest dose recommended for use. The table includes only adverse events occurring at an incidence of at least 1% for zolpidem patients.

Incidence of Treatment-Emergent Adverse Experiences in Long-term Placebo-Controlled Clinical Trials (Percentage of patients reporting)
Body System/ Adverse Event* | Zolpidem (≤10mg) (N=152) | Placebo (N=161)
Autonomic Nervous System
Dry mouth | 3 | 1
Body as a Whole
Allergy | 4 | 1
Back Pain | 3 | 2
Influenza-like symptoms | 2 | -
Chest pain | 1 | -
Fatigue | 1 | 2
Cardiovascular System
Palpitation | 2 | -
Central and Peripheral Nervous System
Headache | 19 | 22
Drowsiness | 8 | 5
Dizziness | 5 | 1
Lethargy | 3 | 1
Drugged feeling | 3 | -
Lightheadedness | 2 | 1
Depression | 2 | 1
Abnormal dreams | 1 | -
Amnesia | 1 | -
Anxiety | 1 | 1
Nervousness | 1 | 3
Sleep disorder | 1 | -
Gastrointestinal System
Nausea | 6 | 6
Dyspepsia | 5 | 6
Diarrhea | 3 | 2
Abdominal pain | 2 | 2
Constipation | 2 | 1
Anorexia | 1 | 1
Vomiting | 1 | 1
Immunologic System
Infection | 1 | 1
Musculoskeletal System
Myalgia | 7 | 7
Arthralgia | 4 | 4
Respiratory System
Upper respiratory infection | 5 | 6
Sinusitis | 4 | 2
Pharyngitis | 3 | 1
Rhinitis | 1 | 3
Skin and Appendages
Rash | 2 | 1
Urogenital System
Urinary tract infection | 2 | 2
*Events reported by at least 1% of patients treated with zolpidem tartrate tablets

Dose relationship for adverse events: There is evidence from dose comparison trials suggesting a dose relationship for many of the adverse events associated with zolpidem use, particularly for certain CNS and gastrointestinal adverse events.

Adverse event incidence across the entire preapproval database: Zolpidem tartrate tablets were administered to 3,660 subjects in clinical trials throughout the U.S., Canada, and Europe. Treatment-emergent adverse events associated with clinical trial participation were recorded by clinical investigators using terminology of their own choosing. To provide a meaningful estimate of the proportion of individuals experiencing treatment-emergent adverse events, similar types of untoward events were grouped into a smaller number of standardized event categories and classified utilizing a modified World Health Organization (WHO) dictionary of preferred terms. The frequencies presented, therefore, represent the proportions of the 3,660 individuals exposed to zolpidem, at all doses, who experienced an event of the type cited on at least one occasion while receiving zolpidem. All reported treatment-emergent adverse events are included, except those already listed in the table above of adverse events in placebo controlled studies, those coding terms that are so general as to be uninformative, and those events where a drug cause was remote. It is important to emphasize that, although the events reported did occur during treatment with zolpidem tartrate tablets, they were not necessarily caused by it.

Adverse events are further classified within body system categories and enumerated in order of decreasing frequency using the following definitions: frequent adverse events are defined as those occurring in greater than 1/100 subjects; infrequent adverse events are those occurring in 1/100 to 1/1,000 patients; rare events are those occurring in less than 1/1,000 patients.

Autonomic nervous system: Infrequent: increased sweating, pallor, postural hypotension, syncope. Rare: abnormal accommodation, altered saliva, flushing, glaucoma, hypotension, impotence, increased saliva, tenesmus.

Body as a whole: Frequent: asthenia. Infrequent: edema, falling, fever, malaise, trauma. Rare: allergic reaction, allergy aggravated, anaphylactic shock, face edema, hot flashes, increased ESR, pain, restless legs, rigors, tolerance increased, weight decrease.

Cardiovascular system: Infrequent: cerebrovascular disorder, hypertension, tachycardia. Rare: angina pectoris, arrhythmia, arteritis, circulatory failure, extrasystoles, hypertension aggravated, myocardial infarction, phlebitis, pulmonary embolism, pulmonary edema, varicose veins, ventricular tachycardia.

Central and peripheral nervous system: Frequent: ataxia, confusion, euphoria, insomnia, vertigo. Infrequent: agitation, decreased cognition, detached, difficulty concentrating, dysarthria, emotional lability, hallucination, hypoesthesia, illusion, leg cramps, migraine, paresthesia, sleeping (after daytime dosing), speech disorder, stupor, tremor. Rare: abnormal gait, abnormal thinking, aggressive reaction, apathy, appetite increased, decreased libido, delusion, dementia, depersonalization, dysphasia, feeling strange, hypokinesia, hypotonia, hysteria, intoxicated feeling, manic reaction, neuralgia, neuritis, neuropathy, neurosis, panic attacks, paresis, personality disorder, somnambulism, suicide attempts, tetany, yawning.

Gastrointestinal system: Frequent: hiccup. Infrequent: constipation, dysphagia, flatulence, gastroenteritis. Rare: enteritis, eructation, esophagospasm, gastritis, hemorrhoids, intestinal obstruction, rectal hemorrhage, tooth caries.

Hematologic and lymphatic system: Rare: anemia, hyperhemoglobinemia, leukopenia, lymphadenopathy, macrocytic anemia, purpura, thrombosis.

Immunologic system: Rare: abscess, herpes simplex, herpes zoster, otitis externa, otitis media.

Liver and biliary system: Infrequent: abnormal hepatic function, increased SGPT. Rare: bilirubinemia, increased SGOT.

Metabolic and nutritional: Infrequent: hyperglycemia, thirst. Rare: gout, hypercholesteremia, hyperlipidemia, increased alkaline phosphatase, increased BUN, periorbital edema.

Musculoskeletal system: Infrequent: arthritis. Rare: arthrosis, muscle weakness, sciatica, tendinitis.

Reproductive system: Infrequent: menstrual disorder, vaginitis. Rare: breast fibroadenosis, breast neoplasm, breast pain.

Respiratory system: Infrequent: bronchitis, coughing, dyspnea. Rare: bronchospasm, epistaxis, hypoxia, laryngitis, pneumonia.

Skin and appendages: Infrequent: pruritus. Rare: acne, bullous eruption, dermatitis, furunculosis, injection-site inflammation, photosensitivity reaction, urticaria.

Special senses: Frequent: diplopia, vision abnormal. Infrequent: eye irritation, eye pain, scleritis, taste perversion, tinnitus. Rare: conjunctivitis, corneal ulceration, lacrimation abnormal, parosmia, photopsia.

Urogenital system: Infrequent: cystitis, urinary incontinence. Rare: acute renal failure, dysuria, micturition frequency, nocturia, polyuria, pyelonephritis, renal pain, urinary retention.

7 DRUG INTERACTIONS

7.1 CNS-active drugs

Zolpidem tartrate tablets were evaluated in healthy volunteers in single-dose interaction studies for several CNS drugs. A study involving haloperidol and zolpidem revealed no effect of haloperidol on the pharmacokinetics or pharmacodynamics of zolpidem. Imipramine in combination with zolpidem produced no pharmacokinetic interaction other than a 20% decrease in peak levels of imipramine, but there was an additive effect of decreased alertness. Similarly, chlorpromazine in combination with zolpidem produced no pharmacokinetic interaction, but there was an additive effect of decreased alertness and psychomotor performance. The lack of a drug interaction following single-dose administration does not predict a lack following chronic administration.

An additive effect on psychomotor performance between alcohol and zolpidem was demonstrated [see Warnings and Precautions: CNS depressant effects (5.5)].

A single-dose interaction study with zolpidem 10 mg and fluoxetine 20 mg at steady-state levels in male volunteers did not demonstrate any clinically significant pharmacokinetic or pharmacodynamic interactions. When multiple doses of zolpidem and fluoxetine at steady-state concentrations were evaluated in healthy females, the only significant change was a 17% increase in the zolpidem half-life. There was no evidence of an additive effect in psychomotor performance.

Following five consecutive nightly doses of zolpidem 10 mg in the presence of sertraline 50 mg (17 consecutive daily doses, at 7:00 am, in healthy female volunteers), zolpidem Cmax was significantly higher (43%) and Tmax was significantly decreased (53%). Pharmacokinetics of sertraline and N-desmethylsertraline were unaffected by zolpidem.

Since the systematic evaluations of zolpidem tartrate tablets (zolpidem tartrate) in combination with other CNS active drugs have been limited, careful consideration should be given to the pharmacology of any CNS-active drug to be used with zolpidem. Any drug with CNS-depressant effects could potentially enhance the CNS-depressant effects of zolpidem.

7.2 Drugs that affect drug metabolism via cytochrome P450

A randomized, double-blind, crossover interaction study in ten healthy volunteers between itraconazole (200 mg once daily for 4 days) and a single dose of zolpidem (10 mg) given 5 hours after the last dose of itraconazole resulted in a 34% increase in AUC0-∞ of zolpidem. There were no significant pharmacodynamic effects of zolpidem on subjective drowsiness, postural sway, or psychomotor performance.

A randomized, placebo-controlled, crossover interaction study in eight healthy female volunteers between 5 consecutive daily doses of rifampin (600 mg) and a single dose of zolpidem (20 mg) given 17 hours after the last dose of rifampin showed significant reductions of the AUC (–73%), Cmax (–58%), and T1/2 (–36%) of zolpidem together with significant reductions in the pharmacodynamic effects of zolpidem.

7.3 Other drugs

A study involving cimetidine/zolpidem and ranitidine/ zolpidem combinations revealed no effect of either drug on the pharmacokinetics or pharmacodynamics of zolpidem. Zolpidem had no effect on digoxin kinetics and did not affect prothrombin time when given with warfarin in normal subjects. Zolpidem's sedative/hypnotic effect was reversed by flumazenil; however, no significant alterations in zolpidem pharmacokinetics were found.

8 USE IN SPECIFIC POPULATIONS

8.1 Pregnancy

Teratogenic effects: Pregnancy Category C

Zolpidem tartrate was administered to pregnant Sprague-Dawley rats by oral gavage during the period of organogenesis at doses of 4, 20, or 100 mg based/kg/day. Adverse maternal and embryo/fetal effects occurred at doses of 20 mg base/kg and higher, manifesting as dose-related lethargy and ataxia in pregnant rats while examination of fetal skull bones revealed a doserelated-trend toward incomplete ossification. Teratogenicity was not observed at any dose level. The no-effect dose of zolpidem for maternal and embryofetal toxicity was 4 mg base/kg/day (between 4 to 5 times the MRHD of zolpidem tartrate tablets on a mg/m^2 basis).

Administration of zolpidem tartrate to pregnant Himalayan Albino rabbits at doses of 1, 4, or 16 mg base/kg/day by oral gavage (over 35 times the MRHD of zolpidem tartrate tablets on a mg/m^2 basis) during the period of organogenesis produced dose-related maternal sedation and decreased maternal body weight gain at all doses. At the high dose of 16 mg base/kg, there was an increase in postimplantation fetal loss and under-ossification of sternebrae in viable fetuses. Teratogenicity was not observed at any dose level. The no-effect dose of zolpidem for maternal toxicity was below 1 mg base/kg/day (< 2-times the MRHD of zolpidem tartrate tablets on a mg/m^2 basis). The no-effect dose for embryofetal toxicity was 4 mg base/kg/day (between 9 and 10 times the MRHD of zolpidem tartrate tablets on a mg/m^2 basis).

Administration of zolpidem tartrate at doses of 4, 20, or 100 mg base/kg/day to pregnant Sprague-Dawley rats starting on Day 15 of gestation and continuing through Day 21 of the postnatal lactation period produced dose-dependent lethargy and ataxia in dams at doses of 20 mg base/kg and higher. Decreased maternal body weight gain as well as evidence on nonsecreting mammary glands and a single incidence of maternal death was observed at 100 mg base/kg. Effects observed on rat pups included decreased body weight with maternal doses of 20 mg base/kg and higher and decreased pup survival at maternal doses of 100 mg base/kg. The noeffect dose for maternal and offspring toxicity was 4 mg base/kg (between 4 to 5 times the MRHD of zolpidem tartrate tablets on a mg/m^2 basis).

There are no adequate and well-controlled studies in pregnant women. Zolpidem tartrate tablets should be used during pregnancy only if the potential benefit justifies the potential risk to the fetus.

NONTERATOGENIC EFFECTS

Nonteratogenic effects. Studies to assess the effects on children whose mothers took zolpidem during pregnancy have not been conducted. However, children born of mothers taking sedative/hypnotic drugs may be at some risk for withdrawal symptoms from the drug during the postnatal period. In addition, neonatal flaccidity has been reported in infants born of mothers who received sedative/hypnotic drugs during pregnancy.

8.2 Labor and delivery

Zolpidem tartrate tablets have no established use in labor and delivery.

8.3 Nursing mothers

Studies in lactating mothers indicate that the half-life of zolpidem is similar to that in young normal volunteers (2.6± 0.3 hr). Between 0.004 and 0.019% of the total administered dose is excreted into milk, but the effect of zolpidem on the infant is unknown.

In addition, in a rat study, zolpidem inhibited the secretion of milk. The no-effect dose was 4 mg base/kg or 6 times the recommended human dose in mg/m^2.

The use of zolpidem tartrate tablets in nursing mothers is not recommended.

8.4 Pediatric use

Safety and effectiveness of zolpidem have not been established in pediatric patients.

In an 8-week controlled study, 201 pediatric patients (aged 6-17 years) with insomnia associated with attention-deficit/hyperactivity disorder (90% of the patients were using psychoanaleptics), were treated with an oral solution of zolpidem, 0.25 mg/kg/day, up to a maximum of 10 mg/day (n=136), or placebo (n = 65). Zolpidem did not significantly decrease latency to persistent sleep, compared to placebo, as measured by polysomnography after 4 weeks of treatment. Psychiatric and nervous system disorders comprised the most frequent (> 5%) treatment emergent adverse events observed with zolpidem versus placebo and included dizziness (23.5% vs. 1.5%), headache (12.5% vs. 9.2%), and hallucinations (7.4% vs. 0%) [see Warnings and Precautions: Special Populations (5.6)]. Ten patients on zolpidem (7.4%) discontinued treatment due to an adverse event.

8.5 Geriatric use

A total of 154 patients in U.S. controlled clinical trials and 897 patients in non-U.S. clinical trials who received zolpidem were ≥60 years of age. For a pool of U.S. patients receiving zolpidem at doses of ≤10 mg or placebo, there were three adverse events occurring at an incidence of at least 3% for zolpidem and for which the zolpidem incidence was at least twice the placebo incidence (ie, they could be considered drug related).

Adverse Event | Zolpidem | Placebo
Dizziness | 3% | 0%
Drowsiness | 5% | 2%
Diarrhea | 3% | 1%

A total of 30/1,959 (1.5%) non-U.S. patients receiving zolpidem reported falls, including 28/30 (93%) who were ≥70 years of age. Of these 28 patients, 23 (82%) were receiving zolpidem doses >10 mg. A total of 24/1,959 (1.2%) non-U.S. patients receiving zolpidem reported confusion, including 18/24 (75%) who were ≥70 years of age. Of these 18 patients, 14 (78%) were receiving zolpidem doses >10 mg.

The recommended dose of zolpidem tartrate tablets is 5 mg in elderly to decrease the possibility of side effects [see Dosage and Administration (2) and Warnings and Precautions (5)].

9 DRUG ABUSE AND DEPENDENCE

9.1 Controlled substance

Zolpidem tartrate is classified as a Schedule IV controlled substance by federal regulation.

9.2 Abuse

Abuse and addiction are separate and distinct from physical dependence and tolerance. Abuse is characterized by misuse of the drug for non-medical purposes, often in combination with other psychoactive substances. Physical dependence is a state of adaptation that is manifested by a specific withdrawal syndrome that can be produced by abrupt cessation, rapid dose reduction, decreasing blood level of the drug, and/or administration of an antagonist. Tolerance is a state of adaptation in which exposure to a drug induces changes that result in a diminution of one or more of the drug effects over time. Tolerance may occur to both desired and undesired effects of drugs and may develop at different rates for different effects.

Addiction is a primary, chronic, neurobiological disease with genetic, psychosocial, and environmental factors influencing its development and manifestations. It is characterized by behaviors that include one or more of the following: impaired control over drug use, compulsive use, continued use despite harm, and craving. Drug addiction is a treatable disease, using a multidisciplinary approach, but relapse is common.

Studies of abuse potential in former drug abusers found that the effects of single doses of zolpidem tartrate tablets 40 mg were similar, but not identical, to diazepam 20 mg, while zolpidem tartrate 10 mg was difficult to distinguish from placebo.

9.3 Dependence

Sedative/hypnotics have produced withdrawal signs and symptoms following abrupt discontinuation. These reported symptoms range from mild dysphoria and insomnia to a withdrawal syndrome that may include abdominal and muscle cramps, vomiting, sweating, tremors, and convulsions. The U.S. clinical trial experience from zolpidem does not reveal any clear evidence for withdrawal syndrome. Nevertheless, the following adverse events included in DSM-III-R criteria for uncomplicated sedative/hypnotic withdrawal were reported during U.S. clinical trials following placebo substitution occurring within 48 hours following last zolpidem treatment: fatigue, nausea, flushing, lightheadedness, uncontrolled crying, emesis, stomach cramps, panic attack, nervousness, and abdominal discomfort. These reported adverse events occurred at an incidence of 1% or less. However, available data cannot provide a reliable estimate of the incidence, if any, of dependence during treatment at recommended doses. Rare post-marketing reports of abuse, dependence and withdrawal have been received.

Because persons with a history of addiction to, or abuse of, drugs or alcohol are at increased risk of habituation and dependence, they should be under careful surveillance when receiving zolpidem or any other hypnotic.

10 OVERDOSAGE

10.1 Signs and symptoms

In European postmarketing reports of overdose with zolpidem alone, impairment of consciousness has ranged from somnolence to light coma. There was one case each of cardiovascular and respiratory compromise. Individuals have fully recovered from zolpidem tartrate overdoses up to 400 mg (40 times the maximum recommended dose). Overdose cases involving multiple CNS-depressant agents, including zolpidem, have resulted in more severe symptomatology, including fatal outcomes.

10.2 Recommended treatment

General symptomatic and supportive measures should be used along with immediate gastric lavage where appropriate. Intravenous fluids should be administered as needed. Flumazenil may be useful. As in all cases of drug overdose, respiration, pulse, blood pressure, and other appropriate signs should be monitored and general supportive measures employed. Hypotension and CNS depression should be monitored and treated by appropriate medical intervention. Sedating drugs should be withheld following zolpidem overdosage, even if excitation occurs. The value of dialysis in the treatment of overdosage has not been determined, although hemodialysis studies in patients with renal failure receiving therapeutic doses have demonstrated that zolpidem is not dialyzable.

Poison control center: As with the management of all overdosage, the possibility of multiple drug ingestion should be considered. The physician may wish to consider contacting a poison control center for up-to-date information on the management of hypnotic drug product overdosage.

11 DESCRIPTION

Zolpidem tartrate is a non-benzodiazepine hypnotic of the imidazopyridine class and is available in 5 mg and 10 mg strength tablets for oral administration.

Chemically, zolpidem is N,N,6-trimethyl-2-p-tolylimidazo[1,2-a] pyridine-3-acetamide L-(+)-tartrate (2:1). It has the following structure:

Zolpidem tartrate is a white to off-white crystalline powder that is sparingly soluble in water, alcohol, and propylene glycol. It has a molecular weight of 764.88.

Each zolpidem tartrate tablet includes the following inactive ingredients: lactose, microcrystalline cellulose, hydroxypropyl cellulose, croscarmellose sodium, magnesium stearate, hypromellose, polyethylene glycol, and titanium dioxide.

12 CLINICAL PHARMACOLOGY

12.1 Mechanism of action

Subunit modulation of the GABAA receptor chloride channel macromolecular complex is hypothesized to be responsible for sedative, anticonvulsant, anxiolytic, and myorelaxant drug properties. The major modulatory site of the GABAA receptor complex is located on its alpha (α) subunit and is referred to as the benzodiazepine (BZ) or omega (ω) receptor. At least three subtypes of the (ω) receptor have been identified.

While zolpidem is a hypnotic agent with a chemical structure unrelated to benzodiazepines, barbiturates, or other drugs with known hypnotic properties, it interacts with a GABA-BZ receptor complex and shares some of the pharmacological properties of the benzodiazepines. In contrast to the benzodiazepines, which non-selectively bind to and activate all (ω) receptor subtypes, zolpidem in vitro binds the (ω1) receptor preferentially with a high affinity ratio of the α1/ α5 subunits. The (ω1) receptor is found primarily on the Lamina IV of the sensorimotor cortical regions, substantia nigra (parsreticulata), cerebellum molecular layer, olfactory bulb, ventral thalamic complex, pons, inferior colliculus, and globus pallidus. This selective binding of zolpidem on the (ω1) receptor is not absolute, but it may explain the relative absence of myorelaxant and anticonvulsant effects in animal studies as well as the preservation of deep sleep (stages 3 and 4) in human studies of zolpidem at hypnotic doses.

12.3 Pharmacokinetics

The pharmacokinetic profile of zolpidem tartrate tablets is characterized by rapid absorption from the GI tract and a short elimination half-life (T1/2) in healthy subjects.

In a single-dose crossover study in 45 healthy subjects administered 5 and 10 mg zolpidem tartrate tablets, the mean peak concentrations (Cmax) were 59 (range: 29 to 113) and 121 (range: 58 to 272) ng/mL, respectively, occurring at a mean time (Tmax) of 1.6 hours for both. The mean zolpidem tartrate tablets elimination half-life was 2.6 (range: 1.4 to 4.5) and 2.5 (range: 1.4 to 3.8) hours, for the 5 and 10 mg tablets, respectively. Zolpidem tartrate is converted to inactive metabolites that are eliminated primarily by renal excretion. Zolpidem tartrate demonstrated linear kinetics in the dose range of 5 to 20 mg. Total protein binding was found to be 92.5 ± 0.1% and remained constant, independent of concentration between 40 and 790 ng/mL. Zolpidem did not accumulate in young adults following nightly dosing with 20 mg zolpidem tartrate tablets for 2 weeks.

A food-effect study in 30 healthy male volunteers compared the pharmacokinetics of zolpidem tartrate tablets 10 mg when administered while fasting or 20 minutes after a meal. Results demonstrated that with food, mean AUC and Cmax were decreased by 15% and 25%, respectively, while mean Tmax was prolonged by 60% (from 1.4 to 2.2hr). The half-life remained unchanged. These results suggest that, for faster sleep onset, zolpidem tartrate tablets should not be administered with or immediately after a meal.

In the elderly, the dose for zolpidem tartrate tablets should be 5 mg [see Warnings and Precautions (5) and Dosage and Administration (2)]. This recommendation is based on several studies in which the mean Cmax, T1/2, and AUC were significantly increased when compared to results in young adults. In one study of eight elderly subjects (>70 years), the means for Cmax, T1/2, and AUC significantly increased by 50% (255 vs 384 ng/mL), 32% (2.2 vs 2.9 hr), and 64% (955 vs 1,562 ng·hr/mL), respectively, as compared to younger adults (20 to 40 years) following a single 20 mg oral dose. Zolpidem tartrate tablets do not accumulate in elderly subjects following nightly oral dosing of 10 mg for 1 week.

The pharmacokinetics of zolpidem tartrate tablets in eight patients with chronic hepatic insufficiency were compared to results in healthy subjects. Following a single 20 mg oral zolpidem dose, mean Cmax and AUC were found to be two times (250 vs 499 ng/mL) and five times (788 vs 4,203 ng·hr/mL) higher, respectively, in hepatically compromised patients. Tmax did not change. The mean half-life in cirrhotic patients of 9.9 hr (range: 4.1 to 25.8 hr) was greater than that observed in normals of 2.2 hr (range: 1.6 to 2.4 hr). Dosing should be modified accordingly in patients with hepatic insufficiency [see Warnings and Precautions (5) and Dosage and Administration (2)].

The pharmacokinetics of zolpidem tartrate were studied in 11 patients with end-stage renal failure (mean ClCr = 6.5 ± 1.5 mL/min) undergoing hemodialysis three times a week, who were dosed with zolpidem 10 mg orally each day for 14 or 21 days. No statistically significant differences were observed for Cmax, Tmax, half-life, and AUC between the first and last day of drug administration when baseline concentration adjustments were made. On day 1, Cmax was 172 ± 29 ng/mL (range: 46 to 344 ng/mL). After repeated dosing for 14 or 21 days, Cmax was 203± 32 ng/mL (range: 28 to 316 ng/mL). On day 1, Tmax was 1.7 ± 0.3 hr (range: 0.5 to 3.0 hr); after repeated dosing Tmax was 0.8 ± 0.2 hr (range: 0.5 to 2.0 hr). This variation is accounted for by noting that last-day serum sampling began 10 hours after the previous dose, rather than after 24 hours. This resulted in residual drug concentration and a shorter period to reach maximal serum concentration. On day 1, T1/2 was 2.4 ± 0.4 hr (range: 0.4 to 5.1 hr). After repeated dosing, T1/2 was 2.5 ± 0.4 hr (range: 0.7 to 4.2 hr). AUC was 796 ± 159 ng·hr/mL after the first dose and 818 ± 170 ng·hr/mL after repeated dosing. Zolpidem was not hemodialyzable. No accumulation of unchanged drug appeared after 14 or 21 days. Zolpidem tartrate pharmacokinetics was not significantly different in renally impaired patients. No dosage adjustment is necessary in patients with compromised renal function. As a general precaution, these patients should be closely monitored.

Postulated relationship between elimination rate of hypnotics and their profile of common untoward effects: The type and duration of hypnotic effects and the profile of unwanted effects during administration of hypnotic drugs may be influenced by the biologic half-life of administered drug and any active metabolites formed. When half-lives are long, drug or metabolites may accumulate during periods of nightly administration and be associated with impairment of cognitive and/or motor performance during waking hours; the possibility of interaction with other psychoactive drugs or alcohol will be enhanced. In contrast, if half-lives, including half-lives of active metabolites, are short, drug and metabolites will be cleared before the next dose is ingested, and carryover effects related to excessive sedation or CNS depression should be minimal or absent. Zolpidem tartrate tablets have a short half-life and no active metabolites. During nightly use for an extended period, pharmacodynamic tolerance or adaptation to some effects of hypnotics may develop. If the drug has a short elimination half-life, it is possible that a relative deficiency of the drug or its active metabolites (ie, in relationship to the receptor site) may occur at some point in the interval between each night's use. This sequence of events may account for two clinical findings reported to occur after several weeks of nightly use of other rapidly eliminated hypnotics, namely, increased wakefulness during the last third of the night, and the appearance of increased signs of daytime anxiety. Increased wakefulness during the last third of the night as measured by polysomnography has not been observed in clinical trials with zolpidem tartrate tablets.

13 NONCLINICAL TOXICOLOGY

13.1 Carcinogenesis, mutagenesis, impairment of fertility

Carcinogenesis: Zolpidem was administered to rats and mice for 2 years at dietary dosages of 4, 18, and 80 mg/kg/day. In mice, these doses are 26 to 520 times or 2 to 35 times the maximum 10 mg human dose on a mg/kg or mg/m^2 basis, respectively. In rats these doses are 43 to 876 times or 6 to 115 times the maximum 10 mg human dose on a mg/kg or mg/m^2 basis, respectively. No evidence of carcinogenic potential was observed in mice. Renal liposarcomas were seen in 4/100 rats (3 males, 1 female) receiving 80 mg/kg/day and a renal lipoma was observed in one male rat at the 18 mg/kg/day dose. Incidence rates of lipoma and liposarcoma for zolpidem were comparable to those seen in historical controls and the tumor findings are thought to be a spontaneous occurrence.

Mutagenesis: Zolpidem did not have mutagenic activity in several tests including the Ames test, genotoxicity in mouse lymphoma cells in vitro, chromosomal aberrations in cultured human lymphocytes, unscheduled DNA synthesis in rat hepatocytes in vitro, and the micronucleus test in mice.

Impairment of fertility: In a rat reproduction study, the high dose (100 mg base/kg) of zolpidem resulted in irregular estrus cycles and prolonged precoital intervals, but there was no effect on male or female fertility after daily oral doses of 4 to 100 mg base/kg or 5 to 130 times the recommended human dose in mg/m^2. No effects on any other fertility parameters were noted.

14 CLINICAL STUDIES

14.1 Transient insomnia

Normal adults experiencing transient insomnia (n = 462) during the first night in a sleep laboratory were evaluated in a double-blind, parallel group, single-night trial comparing two doses of zolpidem (7.5 and 10 mg) and placebo. Both zolpidem doses were superior to placebo on objective (polysomnographic) measures of sleep latency, sleep duration, and number of awakenings.

Normal elderly adults (mean age 68) experiencing transient insomnia (n = 35) during the first two nights in a sleep laboratory were evaluated in a double-blind, crossover, 2-night trial comparing four doses of zolpidem (5, 10, 15 and 20 mg) and placebo. All zolpidem doses were superior to placebo on the two primary PSG parameters (sleep latency and efficiency) and all four subjective outcome measures (sleep duration, sleep latency, number of awakenings, and sleep quality).

14.2 Chronic insomnia

Zolpidem was evaluated in two controlled studies for the treatment of patients with chronic insomnia (most closely resembling primary insomnia, as defined in the APA Diagnostic and Statistical Manual of Mental Disorders, DSM-IV™). Adult outpatients with chronic insomnia (n= 75) were evaluated in a double-blind, parallel group, 5-week trial comparing two doses of zolpidem tartrate (10 and 15 mg) and placebo. On objective (polysomnographic) measures of sleep latency and sleep efficiency, zolpidem 15 mg was superior to placebo for all 5 weeks; zolpidem 10 mg was superior to placebo on sleep latency for the first 4 weeks and on sleep efficiency for weeks 2 and 4. Zolpidem was comparable to placebo on number of awakenings at both doses studied.

Adult outpatients (n=141) with chronic insomnia were also evaluated, in a double-blind, parallel group, 4-week trial comparing two doses of zolpidem (10 and 15 mg) and placebo. Zolpidem 10 mg was superior to placebo on a subjective measure of sleep latency for all 4 weeks, and on subjective measures of total sleep time, number of awakenings, and sleep quality for the first treatment week. Zolpidem 15 mg was superior to placebo on a subjective measure of total sleep latency for the first 3 weeks, on a subjective measure of total sleep time for the first week, and on number of awakenings and sleep quality for the first 2 weeks.

14.3 Studies Pertinent To Safety Concerns For Sedative/Hypnotic Drugs

Next-day residual effects: Next-day residual effects of zolpidem tartrate tablets were evaluated in seven studies involving normal volunteers. In three studies in adults (including one study in a phase advance model of transient insomnia) and in one study in elderly subjects, a small but statistically significant decrease in performance was observed in the Digit Symbol Substitution Test (DSST) when compared to placebo. Studies of zolpidem tartrate tablets in non-elderly patients with insomnia did not detect evidence of next-day residual effects using the DSST, the Multiple Sleep Latency Test (MSLT), and patient ratings of alertness.

Rebound effects: There was no objective (polysomnographic) evidence of rebound insomnia at recommended doses seen in studies evaluating sleep on the nights following discontinuation of zolpidem tartrate tablets (zolpidem tartrate). There was subjective evidence of impaired sleep in the elderly on the first post-treatment night at doses above the recommended elderly dose of 5 mg.

Memory impairment: Controlled studies in adults utilizing objective measures of memory yielded no consistent evidence of next-day memory impairment following the administration of zolpidem tartrate tablets. However, in one study involving zolpidem doses of 10 and 20 mg, there was a significant decrease in next-morning recall of information presented to subjects during peak drug effect (90 minutes post-dose), ie, these subjects experienced anterograde amnesia. There was also subjective evidence from adverse event data for anterograde amnesia occurring in association with the administration of zolpidem tartrate tablets, predominantly at doses above 10 mg.

Effects on sleep stages: In studies that measured the percentage of sleep time spent in each sleep stage, zolpidem tartrate tablets has generally been shown to preserve sleep stages. Sleep time spent in stages 3 and 4 (deep sleep) was found comparable to placebo with only inconsistent, minor changes in REM (paradoxical) sleep at the recommended dose.

16 HOW SUPPLIED/STORAGE AND HANDLING

16.1 How Supplied

Zolpidem tartrate tablets 5-mg are white round film-coated tablets engraved with “CST 8”

NDC Number Size

063126-231-30 Bottle of 30

063126-231-01 Bottle of 1,000

Zolpidem tartrate tablets 10-mg are white round film-coated tablets engraved with “B”

NDC Number Size

063126-232-30 Bottle of 30

063126-232-01 Bottle of 1,000

16.2 Storage and handling

Store at controlled room temperature 20° to 25°C (68° to 77°F)

Rx only

Manufactured by:

Yung Shin Pharmaceutical Industrial Co., Ltd.
Tachia, Taichung
Taiwan, ROC

Revision: April 2007

17 PATIENT COUNSELING INFORMATION

17.1 General:

Patient information is printed at the end of this insert. To assure safe and effective use of zolpidem tartrate tablets, this information and instructions provided in the patient information section should be discussed with patients.

17.2 FDA-approved patient labeling

Your doctor has prescribed zolpidem tartrate tablets to help you sleep. The following information is intended to guide you in the safe use of this medicine. It is not meant to take the place of your doctor's instructions. If you have any questions about zolpidem tartrate tablets be sure to ask your doctor or pharmacist.

Zolpidem tartrate tablets are used to treat different types of sleep problems in adults, such as:

- trouble falling asleep
- waking up too early in the morning
- waking up often during the night

Some people may have more than one of these problems.

Zolpidem tartrate tablets belong to a group of medicines known as the “sedative/hypnotics,” or simply, sleep medicines. There are many different sleep medicines available to help people sleep better. Sleep problems are usually temporary, requiring treatment for only a short time, usually 1 or 2 days up to 1 or 2 weeks. Some people have chronic sleep problems that may require more prolonged use of sleep medicine. However, you should not use these medicines for long periods without talking with your doctor about the risks and benefits of prolonged use.

SIDE EFFECTS

Most common side effects: All medicines have side effects. Most common side effects of sleep medicines include

- drowsiness
- dizziness
- lightheadedness
- difficulty with coordination

You may find that these medicines make you sleepy during the day. How drowsy you feel depends upon how your body reacts to the medicine, which sleep medicine you are taking, and how large a dose your doctor has prescribed. Daytime drowsiness is best avoided by taking the lowest dose possible that will still help you sleep at night. Your doctor will work with you to find the dose of zolpidem tartrate tablets that is best for you.

To manage these side effects while you are taking this medicine:

- When you first start taking zolpidem tartrate tablets or any other sleep medicine until you know whether the medicine will still have some carryover effect in you the next day, use extreme care while doing anything that requires complete alertness, such as driving a car, operating machinery, or piloting an aircraft.
- NEVER drink alcohol while you are being treated with zolpidem tartrate tablets or any sleep medicine. Alcohol can increase the side effects of zolpidem tartrate tablets or any other sleep medicine.
- Do not take any other medicines without asking your doctor first. This includes medicines you can buy without a prescription. Some medicines can cause drowsiness and are best avoided while taking zolpidem tartrate tablets.
- Always take the exact dose of zolpidem tartrate tablets prescribed by your doctor. Never change your dose without talking to your doctor first.

SPECIAL CONCERNS

There are some special problems that may occur while taking sleep medicines.

“Sleep-Driving” and other complex behaviors: There have been reports of people getting out of bed after taking a sleep medicine and driving their cars while not fully awake, often with no memory of the event. If you experience such an event, it should be reported to your doctor immediately, since “sleep-driving” can be dangerous. This behavior is more likely to occur when zolpidem tartrate tablets is taken with alcohol or other drugs such as those for the treatment of depression or anxiety. Other behaviors such as preparing and eating food, making phone calls, or having sex have been reported in people who are not fully awake after taking a sleep medicine. As with “sleep-driving”, people usually do not remember these events.

Memory problems: Sleep medicines may cause a special type of memory loss or “amnesia.” When this occurs, a person may not remember what has happened for several hours after taking the medicine. This is usually not a problem since most people fall asleep after taking the medicine.

Memory loss can be a problem, however, when sleep medicines are taken while traveling, such as during an airplane flight and the person wakes up before the effect of the medicine is gone. This has been called “traveler's amnesia.”

Memory problems are not common while taking zolpidem tartrate tablets. In most instances memory problems can be avoided if you take zolpidem tartrate tablets only when you are able to get a full night's sleep (7 to 8 hours) before you need to be active again. Be sure to talk to your doctor if you think you are having memory problems.

Tolerance: When sleep medicines are used every night for more than a few weeks, they may lose their effectiveness to help you sleep. This is known as “tolerance.'' Sleep medicines should, in most cases, be used only for short periods of time, such as 1 or 2 days and generally no longer than 1 or 2 weeks. If your sleep problems continue, consult your doctor, who will determine whether other measures are needed to overcome your sleep problems.

Dependence: Sleep medicines can cause dependence, especially when these medicines are used regularly for longer than a few weeks or at high doses. Some people develop a need to continue taking their medicines. This is known as dependence or “addiction.”

When people develop dependence, they may have difficulty stopping the sleep medicine. If the medicine is suddenly stopped, the body is not able to function normally and unpleasant symptoms (see Withdrawal) may occur. They may find they have to keep taking the medicine either at the prescribed dose or at increasing doses just to avoid withdrawal symptoms.

All people taking sleep medicines have some risk of becoming dependent on the medicine. However, people who have been dependent on alcohol or other drugs in the past may have a higher chance of becoming addicted to sleep medicines. This possibility must be considered before using these medicines for more than a few weeks.

If you have been addicted to alcohol or drugs in the past, it is important to tell your doctor before starting zolpidem tartrate tablets or any sleep medicine.

Withdrawal: Withdrawal symptoms may occur when sleep medicines are stopped suddenly after being used daily for a long time. In some cases, these symptoms can occur even if the medicine has been used for only a week or two.

In mild cases, withdrawal symptoms may include unpleasant feelings. In more severe cases, abdominal and muscle cramps, vomiting, sweating, shakiness, and rarely, seizures may occur. These more severe withdrawal symptoms are very uncommon.

Another problem that may occur when sleep medicines are stopped is known as “rebound insomnia.” This means that a person may have more trouble sleeping the first few nights after the medicine is stopped than before starting the medicine. If you should experience rebound insomnia, do not get discouraged. This problem usually goes away on its own after 1 or 2 nights.

If you have been taking zolpidem tartrate tablets or any other sleep medicine for more than 1 or 2 weeks, do not stop taking it on your own. Always follow your doctor's directions.

Changes in behavior and thinking: Some people using sleep medicines have experienced unusual changes in their thinking and/or behavior. These effects are not common. However, they have included:

- more outgoing or aggressive behavior than normal
- loss of personal identity
- confusion
- strange behavior
- agitation
- hallucinations
- worsening of depression
- suicidal thoughts

How often these effects occur depends on several factors, such as a person's general health, the use of other medicines, and which sleep medicine is being used. Clinical experience with zolpidem tartrate tablets suggests that it is uncommonly associated with these behavior changes.

It is also important to realize that it is rarely clear whether these behavior changes are caused by the medicine, an illness, or occur on their own. In fact, sleep problems that do not improve may be due to illnesses that were present before the medicine was used. If you or your family notice any changes in your behavior, or if you have any unusual or disturbing thoughts, call your doctor immediately.

Pregnancy: Sleep medicines may cause sedation of the unborn baby when used during the last weeks of pregnancy.

Be sure to tell your doctor if you are pregnant, if you are planning to become pregnant, or if you become pregnant while taking zolpidem tartrate tablets.

Children: Zolpidem tartrate tablets have not been shown to help children fall asleep. Hallucinations, headache and dizziness have all been reported as side effects in children who were given zolpidem tartrate tablets.

SAFE USE OF SLEEPING MEDICINES

To ensure the safe and effective use of zolpidem tartrate tablets or any other sleep medicine, you should observe the following cautions:

1. Zolpidem tartrate tablet is a prescription medicine and should be used ONLY as directed by your doctor. Follow your doctor's instructions about how to take, when to take, and how long to take zolpidem tartrate tablets.
2. Never use zolpidem tartrate tablets or any other sleep medicine for longer than directed by your doctor.
3. If you develop an allergic reaction such as a rash, hives, shortness of breath, or swelling of your tongue or throat when using zolpidem tartrate tablets or any other sleep medicine, discontinue zolpidem tartrate tablets or other sleep medicine immediately and contact your doctor.
4. If you notice any unusual and/or disturbing thoughts or behavior during treatment with zolpidem tartrate tablets or any other sleep medicine, contact your doctor.
5. Tell your doctor about any medicines you may be taking, including medicines you may buy without a prescription. You should also tell your doctor if you drink alcohol. DO NOT use alcohol while taking zolpidem tartrate tablets or any other sleep medicine.
6. Do not take zolpidem tartrate tablets unless you are able to get a full night's sleep before you must be active again. For example, zolpidem tartrate tablets should not be taken on an overnight airplane flight of less than 7 to 8 hours since “traveler's amnesia” may occur.
7. Do not increase the prescribed dose of zolpidem tartrate tablets or any other sleep medicine unless instructed by your doctor.
8. When you first start taking zolpidem tartrate tablets or any other sleep medicine until you know whether the medicine will still have some carryover effect in you the next day, use extreme care while doing anything that requires complete alertness, such as driving a car, operating machinery, or piloting an aircraft.
9. Be aware that you may have more sleeping problems the first night or two after stopping zolpidem tartrate tablets or any other sleep medicine.
10. Be sure to tell your doctor if you are pregnant, if you are planning to become pregnant, or if you become pregnant while taking zolpidem tartrate tablets.
11. As with all prescription medicines, never share zolpidem tartrate tablets or any other sleep medicine with anyone else. Always store zolpidem tartrate tablets or any other sleep medicine in the original container out of reach of children.
12. Zolpidem tartrate tablets work very quickly. You should only take zolpidem tartrate tablets right before going to bed and are ready to go to sleep.

Rx only

Manufactured by:

Yung Shin Pharmaceutical Industrial Co., Ltd.
Tachia, Taichung
Taiwan, ROC

Revision: April 2007